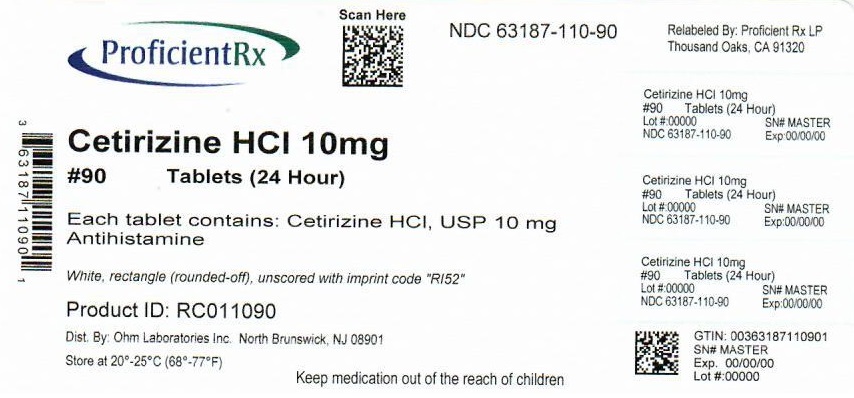 DRUG LABEL: Cetirizine Hydrochloride
NDC: 63187-110 | Form: TABLET
Manufacturer: Proficient Rx LP
Category: otc | Type: HUMAN OTC DRUG LABEL
Date: 20220601

ACTIVE INGREDIENTS: CETIRIZINE HYDROCHLORIDE 10 mg/1 1
INACTIVE INGREDIENTS: POVIDONE, UNSPECIFIED; LACTOSE MONOHYDRATE; MAGNESIUM STEARATE; STARCH, CORN; TALC; TITANIUM DIOXIDE; HYPROMELLOSE, UNSPECIFIED; POLYETHYLENE GLYCOL, UNSPECIFIED

Drug Facts

ACTIVE INGREDIENT (IN EACH TABLET)

Cetirizine HCl, USP 10 mg

PURPOSE

Antihistamine

USES

temporarily relieves these symptoms due to hay fever or other upper respiratory allergies:

- runny nose
- sneezing
- itchy, watery eyes
- itching of the nose or throat

WARNINGS

Do not use

if you have ever had an allergic reaction to this product or any of its ingredients or to an antihistamine containing hydroxyzine.

Ask a doctor before use if you have

liver or kidney disease. Your doctor should determine if you need a different dose.

Ask a doctor or pharmacist before use if you are

taking tranquilizers or sedatives.

When using this product

- drowsiness may occur
- avoid alcoholic drinks
- alcohol, sedatives, and tranquilizers may increase drowsiness
- be careful when driving a motor vehicle or operating machinery

Stop use and ask a doctor if

an allergic reaction to this product occurs. Seek medical help right away.

If pregnant or breast-feeding:

- if breast-feeding: not recommended
- if pregnant: ask a health professional before use.

Keep out of reach of children.

In case of overdose, get medical help or contact a Poison Control Center right away (1-800-222-1222).

DIRECTIONS

adults and children 6 years and over: one 10 mg tablet once daily; do not take more than one 10 mg tablet in 24 hours. A 5 mg product may be appropriate for less severe symptoms.

adults 65 years and over: ask a doctor

children under 6 years of age: ask a doctor

consumers with liver or kidney disease: ask a doctor

OTHER INFORMATION

- TAMPER EVIDENT: DO NOT USE IF IMPRINTED SEAL IS BROKEN OR MISSING FROM BOTTLE.(for bottle cartons/stand-alone labels only)
- TAMPER EVIDENT: DO NOT USE IF BLISTER UNITS ARE TORN, BROKEN OR SHOW ANY SIGNS OF TAMPERING.(for blister cartons only)
- store between 20° to 25° C (68° to 77° F)

INACTIVE INGREDIENTS

corn starch, hypromellose, lactose monohydrate, magnesium stearate, polyethylene glycol, povidone, talc, titanium dioxide

QUESTIONS?

call 1-800-406-7984

KEEP THE CARTON. IT CONTAINS IMPORTANT INFORMATION. SEE END PANEL FOR EXPIRATION DATE.

Distributed by:

Ohm Laboratories Inc.

1385 Livingston Avenue

North Brunswick, NJ 08902

Relabeled by:

Proficient Rx LP

Thousand Oaks, CA 91320

PRINCIPAL DISPLAY PANEL

†Compare to the active ingredient of Zyrtec®

NDC 63187-110-90

Original Prescription Strength

Cetirizine HCl Tablets, 10 mg

Antihistamine

Allergy

Indoor & Outdoor Allergies

24 Hour

Relief of:

- Sneezing
- Runny Nose
- Itchy, Watery Eyes
- Itchy Throat or Nose

90 TABLETS 10 mg EACH

†This product is not manufactured or distributed by McNeil-PPC, Inc., distributor of Zyrtec®. Zyrtec® is a registered trademark of UCB Pharma, S.A.